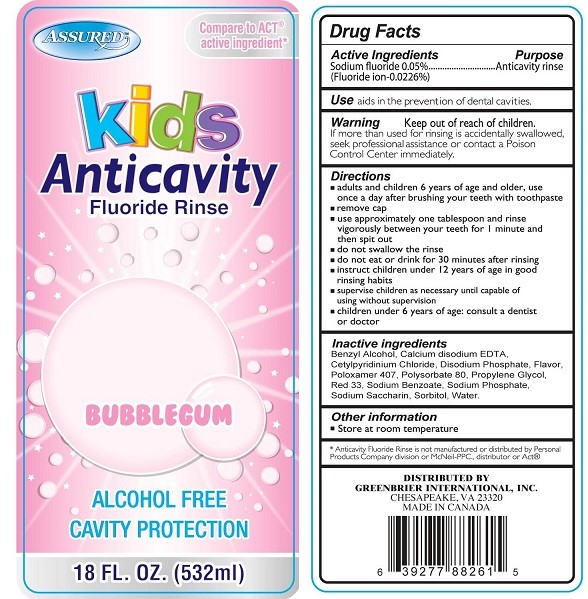 DRUG LABEL: Assured Anticavity Fluoride Kids Bubblegum
NDC: 33992-0015 | Form: RINSE
Manufacturer: Greenbrier International, Inc.
Category: otc | Type: HUMAN OTC DRUG LABEL
Date: 20210823

ACTIVE INGREDIENTS: SODIUM FLUORIDE 0.05 g/100 mL
INACTIVE INGREDIENTS: SODIUM PHOSPHATE; BENZYL ALCOHOL; EDETATE CALCIUM DISODIUM ANHYDROUS; CETYLPYRIDINIUM CHLORIDE; POLOXAMER 407; POLYSORBATE 80; PROPYLENE GLYCOL; D&C RED NO. 33; SODIUM BENZOATE; SODIUM PHOSPHATE DIBASIC DIHYDRATE; SACCHARIN SODIUM; SORBITOL; WATER

Assured Kids Anticavity Fluoride Rinse Bubblegum

Drug Facts

Active Ingredients

Sodium fluoride 0.05% (Fluoride ion-0.0226%)

Purpose

Anticavity rinse

INDICATIONS AND USAGE

Use aids in the prevention of dental cavities.

Warning

Keep out of reach of children. If more than used for rinsing is accidentally swallowed, get medical help or contact a Poison Control Center immediately.

Directions

- adults and children 6 years of age and older, use once a day after brushing your teeth with a toothpaste
- remove cap
- use approximately one tablespoon and rinse vigorously between your teeth for 1 minute and then spit out
- do not swallow the rinse
- do not eat or drink for 30 minutes after rinsing
- instruct children under 12 years of age in good rinsing habits
- supervise children as necessary until capable of using without supervision
- children under 6 years of age: consult a dentist or doctor

INACTIVE INGREDIENT

Inactive ingredients Benzyl Alcohol, Calcium disodium EDTA, Cetylpyridinium Chloride, Disodium Phosphate, Flavor, Poloxamer 407, Polysorbate 80, Propylene Glycol, Red 33, Sodium Benzoate, Sodium Phosphate, Sodium Saccharin, Sorbitol, Water

Other information

- Store at room temperature

*Anticavity Fluoride Rinse is not manufactured or distributed by Personal Products Company division or McNeil-PPC., distributor or Act®

DISTRIBUTED BY GREENBRIER INTERNATIONAL, INC.

CHESAPEAKE, VA 23320

MADE IN CANADA

PACKAGE LABEL

ASSURED™

Compare to ACT® active ingredient*

Kids Anticavity

Fluoride Rinse
BUBBLEGUM

ALCOHOL FREE

CAVITY PROTECTION
18 FL. OZ. (532 mL)